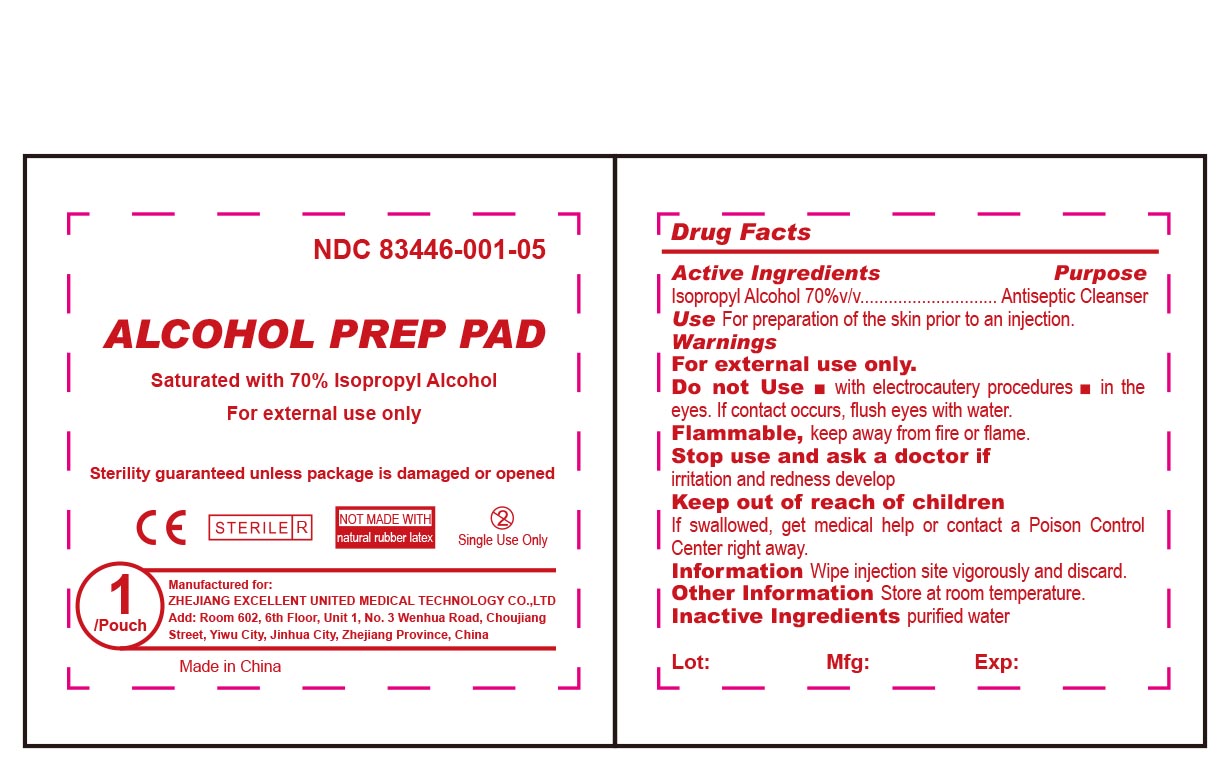 DRUG LABEL: ALCOHOL PREP PADS MEDIUM STERILE
NDC: 83446-001 | Form: CLOTH
Manufacturer: JINHUA JINGDI MEDICAL SUPPLIES CO., LTD
Category: otc | Type: HUMAN OTC DRUG LABEL
Date: 20251231

ACTIVE INGREDIENTS: ISOPROPYL ALCOHOL 70 mL/100 mL
INACTIVE INGREDIENTS: WATER 30 mL/100 mL

ACTIVE INGREDIENT

Isopropyl Alcohol, 70% v/v

DESCRIPTION

Sterility guaranteed unless package is damaged or opened.

Not made with natural rubber latex.

INACTIVE INGREDIENT

Purified Water

PURPOSE

Antiseptic Cleanser.

Use for preparation of the skin prior to an injection.

WARNINGS

For external use only. Flammable, keep away from fire or flame.

KEEP OUT OF REACH OF CHILDREN

If swallowed, get medical help or contact a poison control center right away.

Directions

Wipe injection site vigorosly and discard.

DO NOT USE

- With electrocautery procedures.
- In the eyes. If contact occurs, flush eyes with water.

Stop use and ask a doctor if irritation and redness develop.

OTHER SAFETY INFORMATION

Store at room temperature

DOSAGE AND ADMINISTRATION

Apply topically as needed to cleanse intendend area；
Apply the product to the skin, take the injection or puncture site as the center, slowly rotate from the insideto the outside, and gradually apply the product for two times, the disinfection area should be more than5cmx5cm, and the action time should be 1min.